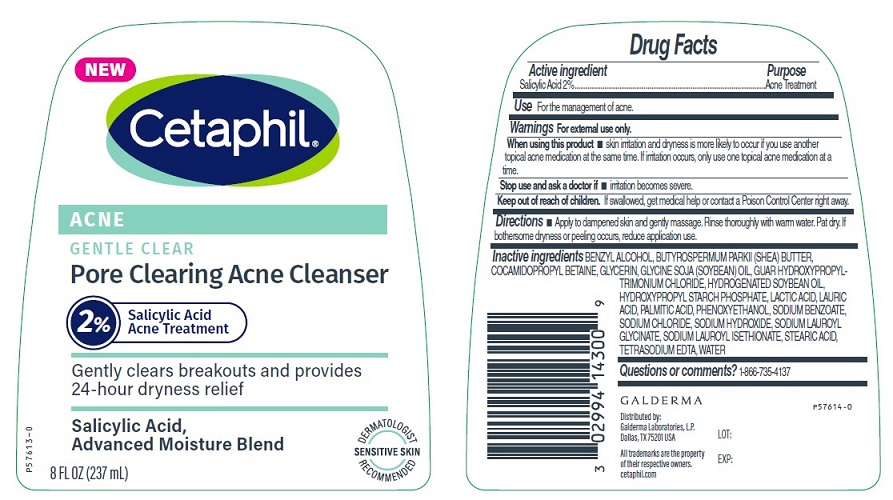 DRUG LABEL: Cetaphil Gentle Clear Pore Clearing Acne Cleanser
NDC: 0299-4143 | Form: GEL
Manufacturer: Galderma Laboratories, L.P.
Category: otc | Type: HUMAN OTC DRUG LABEL
Date: 20240509

ACTIVE INGREDIENTS: Salicylic Acid 20 mg/1 mL
INACTIVE INGREDIENTS: Benzyl Alcohol; Shea Butter; Cocamidopropyl Betaine; Glycerin; Soybean Oil; Guar Hydroxypropyltrimonium Chloride (1.7 Substituents Per Saccharide); Hydrogenated Soybean Oil; Lactic Acid, Unspecified Form; Lauric Acid; Palmitic Acid; Phenoxyethanol; Sodium Benzoate; Sodium Chloride; Sodium Hydroxide; Sodium Lauroyl Glycinate; Sodium Lauroyl Isethionate; Stearic Acid; Edetate Sodium; Water

Drug Facts

Active Ingredient

Salicylic Acid 2%

Purpose

Acne Treatment

Use

For the management of acne

Warnings

For external use only

When using this product

• skin irritation and dryness is more likely to occur if you use another topical acne medication at the same time. If irritation occurs, only use one topical acne medication at a time.

Stop use and ask a doctor if

• irritation becomes severe.

Keep out of reach of children.

If swallowed, get medical help or contact a Poison Control Center right away.

Directions

Apply to dampened skin and gently massage. Rinse thoroughly with warm water. Pat dry. If bothersome dryness or peeling occurs, reduce application use.

Inactive Ingredients

BENZYL ALCOHOL, BUTYROSPERMUM PARKII (SHEA) BUTTER, COCAMIDOPROPYL BETAINE, GLYCERIN, GLYCINE SOJA (SOYBEAN) OIL, GUAR HYDROXYPROPYLTRIMONIUM CHLORIDE, HYDROGENATED SOYBEAN OIL, HYDROXYPROPYL STARCH PHOSPHATE, LACTIC ACID, LAURIC ACID, PALMITIC ACID, PHENOXYETHANOL, SODIUM BENZOATE, SODIUM CHLORIDE, SODIUM HYDROXIDE, SODIUM LAUROYL GLYCINATE, SODIUM LAUROYL ISETHIONATE, STEARIC ACID, TETRASODIUM EDTA, WATER

Questions or comments? 1-866-735-4137

Distributed by:
Galderma Laboratories, L.P.
Dallas, TX 75201 USA
All trademarks are the property
of their respective owners.
cetaphil.com

PRINCIPAL DISPLAY PANEL - 8 FL OZ bottle

NEW
Cetaphil®

ACNE
Gentle Clear
Pore Clearing Acne Cleanser

2% Salicylic Acid Acne Treatment

Gently clears breakouts and provides
24-hour dryness relief

Salicylic Acid
Advanced Moisture Blend

Dermatologist Recommended
Sencitive Skin
8 FL OZ (237 mL)
P57613-0